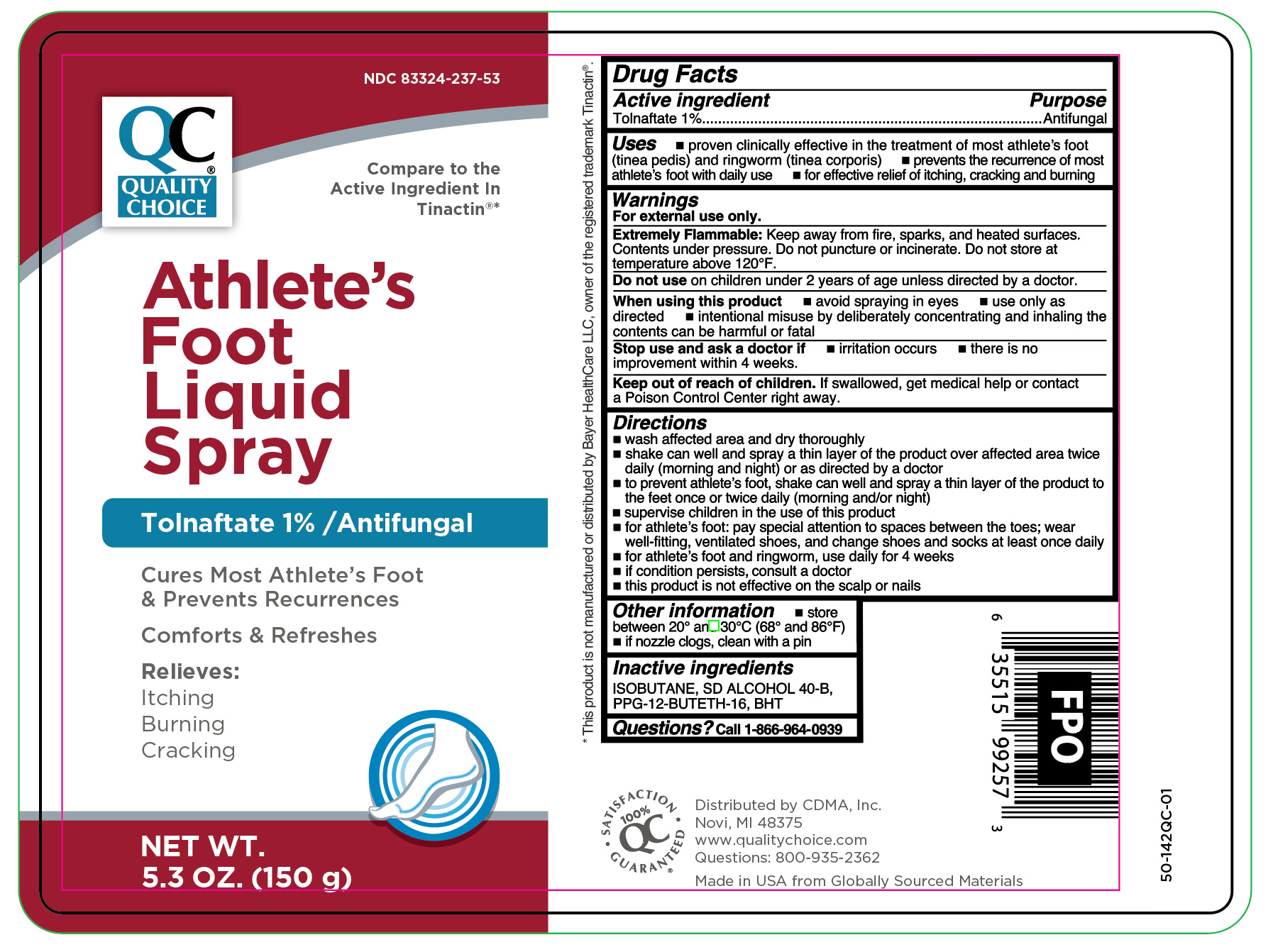 DRUG LABEL: Tolnaftate
NDC: 83324-237 | Form: AEROSOL, SPRAY
Manufacturer: Chain Drug Marketing Association
Category: otc | Type: HUMAN OTC DRUG LABEL
Date: 20251106

ACTIVE INGREDIENTS: TOLNAFTATE 10 mg/1 g
INACTIVE INGREDIENTS: ALCOHOL; ISOBUTANE; PPG-12-BUTETH-16; BUTYLATED HYDROXYTOLUENE

Quality Choice Antifungal Tolnaftate Liquid Spray

Active ingredient

Tolnaftate 1%

Purpose

Antifungal

Uses

- proven clinically effective in the treatment of most athlete's foot (tinea pedis) and ringworm (tinea corporis)
- prevents the recurrence of most athlete's foot with daily use
- for effective relief of itching, cracking and burning

Warnings

For external use only.

Extremely Flammable:

Keep away from fire, sparks, and heated surfaces. Contents under pressure. Do not puncture or incinerate. Do not store at temperature above 120°F.

Do not use

on children under 2 years of age unless directed by a doctor.

When using this product

- avoid spraying in eyes
- use only as directed
- intentional misuse by deliberately concentrating and inhaling the contents can be harmful or fatal

Stop use and ask a doctor if

- irritation occurs
- there is no improvement within 4 weeks

Keep out of reach of children.

If swallowed, get medical help or contact a Poison Control Center right away.

Directions

- wash affected area and dry thoroughly
- shake can well and spray a thin layer of the product over affected area twice daily (morning and night) or as directed by a doctor
- to prevent athlete's foot, shake can well and spray a thin layer of the product to the feet once or twice daily (morning and/or night)
- supervise children in the use of this product
- for athlete's foot: pay special attention to spaces between the toes; wear well-fitting, ventilated shoes, and change shoes and socks at least once daily
- for athlete's foot and ringworm, use daily for 4 weeks
- if condition persists, consult a doctor
- this product is not effective on the scalp or nails

Other information

- store between 20° and 30°C (68° and 86°F)
- if nozzle clogs, clean with a pin

Inactive ingredients

ISOBUTANE, SD ALCOHOL 40-B, PPG-12-BUTETH-16, BHT

Questions?

Call 1-866-964-0939

RECENT MAJOR CHANGES

..

Principal Display Panel

QC

Quality

Choice

Athlete's

Foot

Liquid

Spray

Tolnaftate 1% / Antifungal

Cures Most Athlete's Foot

& Prevents Recurrences

Comforts & Refreshes

Relieves:

Itching

Burning

Cracking

NET WT.

5.3 OZ. (150 g)